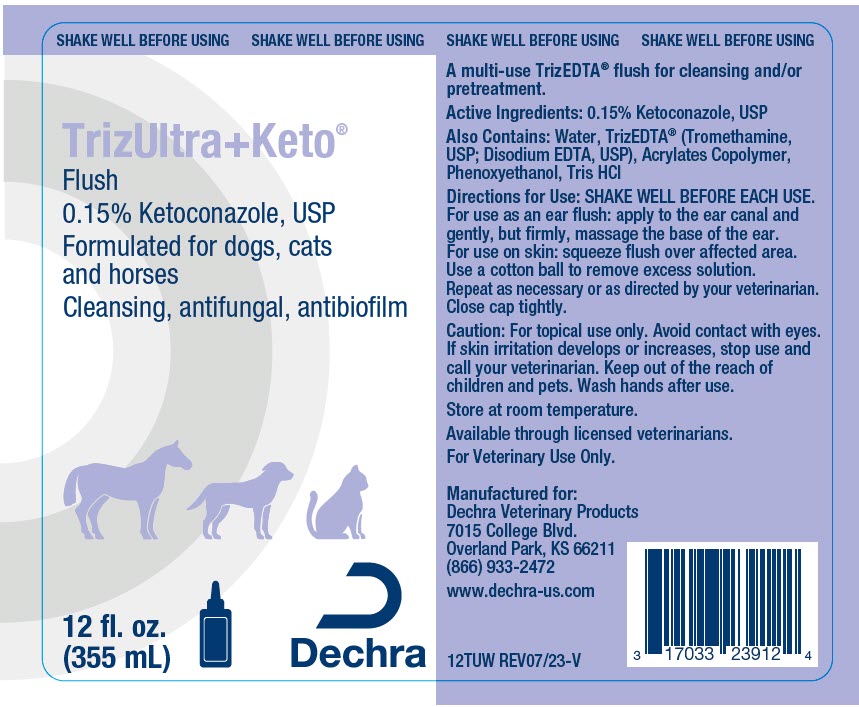 DRUG LABEL: TrizUltra Plus Keto Flush
NDC: 17033-239 | Form: SOLUTION
Manufacturer: Dechra Veterinary Products
Category: animal | Type: OTC ANIMAL DRUG LABEL
Date: 20240223

ACTIVE INGREDIENTS: KETOCONAZOLE 1.5 mg/1 mL

TrizUltra+Keto®
Flush

VETERINARY INDICATIONS

A multi-use TrizEDTA® flush for cleansing and/or pretreatment.

DESCRIPTION

Active Ingredients: 0.15% Ketoconazole, USP

Also Contains: Water, TrizEDTA® (Tromethamine, USP; Disodium EDTA, USP), Acrylates Copolymer, Phenoxyethanol, Tris HCl

DOSAGE AND ADMINISTRATION

Directions for Use: SHAKE WELL BEFORE EACH USE. For use as an ear flush: apply to the ear canal and gently, but firmly, massage the base of the ear. For use on skin: squeeze flush over affected area. Use a cotton ball to remove excess solution. Repeat as necessary or as directed by your veterinarian. Close cap tightly.

SAFE HANDLING WARNING

Caution: For topical use only. Avoid contact with eyes. If skin irritation develops or increases, stop use and call your veterinarian. Keep out of the reach of children and pets. Wash hands after use.

STORAGE AND HANDLING

Store at room temperature.

Manufactured for:
Dechra Veterinary Products
7015 College Blvd.
Overland Park, KS 66211
(866) 933-2472

www.dechra-us.com

12TUW REV07/23-V

PRINCIPAL DISPLAY PANEL - 355 ml Bottle Label

SHAKE WELL BEFORE USING

TrizUltra+Keto®

Flush
0.15% Ketoconazole, USP
Formulated for dogs, cats
and horses
Cleansing, antifungal, antibiofilm

12 fl. oz.
(355 mL)

Dechra